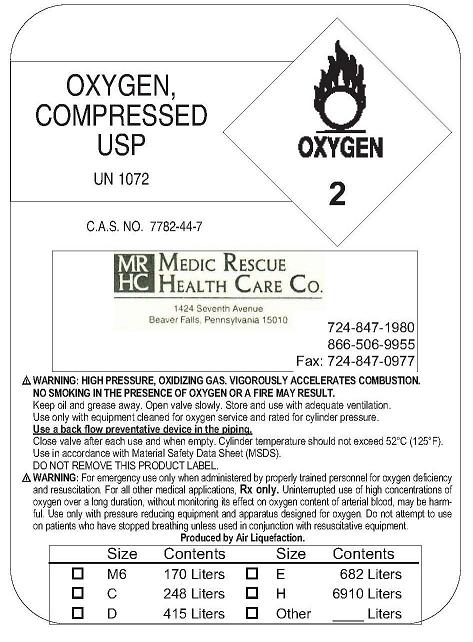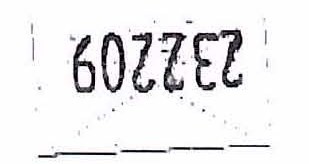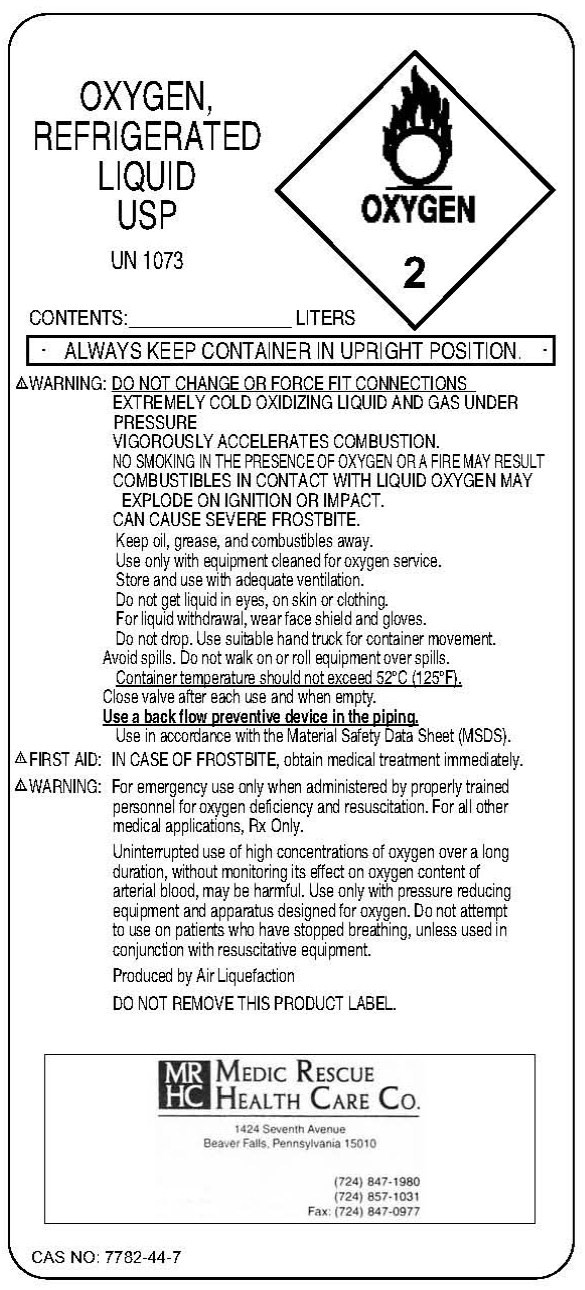 DRUG LABEL: Oxygen
NDC: 57804-1020 | Form: GAS
Manufacturer: Medic Rescue Health Care Company
Category: prescription | Type: HUMAN PRESCRIPTION DRUG LABEL
Date: 20091118

ACTIVE INGREDIENTS: Oxygen 99 L/100 L

Oxygen